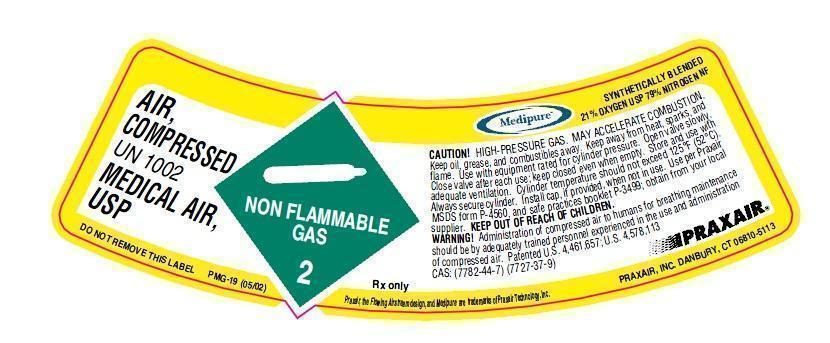 DRUG LABEL: Air
NDC: 59579-016 | Form: GAS
Manufacturer: Praxair Distribution, Inc.
Category: animal | Type: PRESCRIPTION ANIMAL DRUG LABEL
Date: 20211220

ACTIVE INGREDIENTS: Air 1000 mL/1 L

Air-Animal

PACKAGE LABEL

UN1002 AIR, COMPRRESSED MEDICAL AIR, USP CAUTION! HIGH-PRESSURE GAS. MAY ACCELERATE COMBUSTION Keep oil, grease, and combustibles away. Keep away from heat, sparks, and flame. Use with equipment rated for cylinder pressure. Open valve slowly. Close valve after each use; keep closed even when empty. Store and use with adequate ventilation. Cylinder temperature should not exceed 125°F (52°C). Always secure cylinder. Install cap, if provided, when not in use. Use per Praxair MSDS form P-4560, and safe practices booklet P-3499; obtain from your local supplier. KEEP OUT OF REACH OF CHILDREN. WARNING! Administration of compressed air to humans for breathing maintenance should be by adequately trained personnel experienced in the use and administration of compressed air. Patented U.S. 4,461,657; U.S. 4,578,113 Rx only CAS: (7782-44-7) (7727-37-9) DO NOT REMOVE THIS LABEL BY PRAXAIR, INC., DANBURY PMG-19 (05/02) DISTRIBUTED SYNTHETICALLY BLENDED 21% OXYGEN USP 79%NITROGEN NF Praxair, the flowing airstream design and Medipure are trademarks of Praxair Technology, Inc. DISTRIBUTED BY PRAXAIR, INC, DANBURY, CT 06810-5113 DISTRIBUTED BY PRAXAIR, INC.